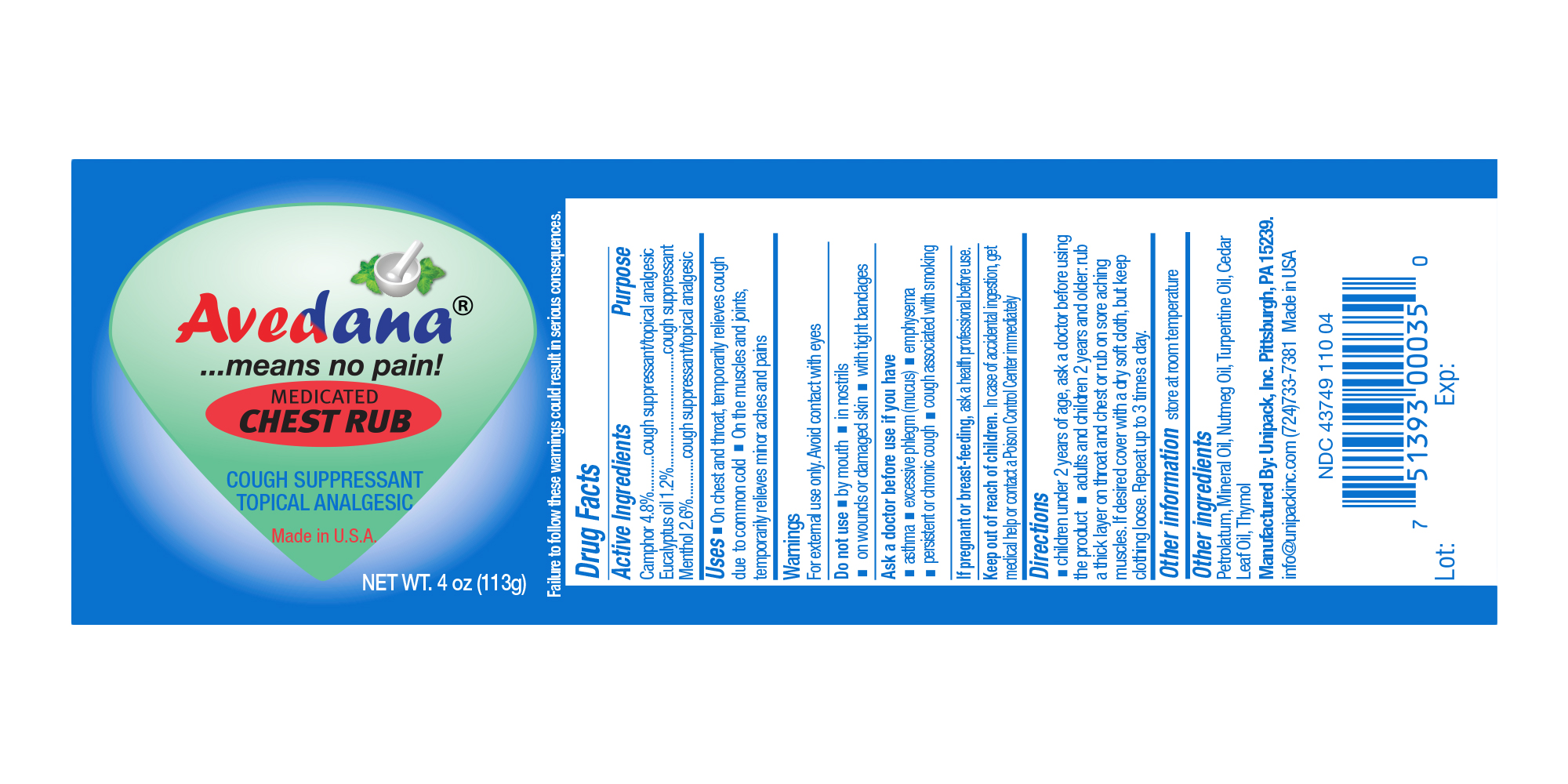 DRUG LABEL: Avedana Medicated Chest Rub
NDC: 43749-110 | Form: OINTMENT
Manufacturer: Unipack LLC
Category: otc | Type: HUMAN OTC DRUG LABEL
Date: 20230118

ACTIVE INGREDIENTS: CAMPHOR (SYNTHETIC) 4.8 g/100 g; EUCALYPTUS OIL 1.2 g/100 g; MENTHOL 2.6 g/100 g
INACTIVE INGREDIENTS: PETROLATUM 91.05 g/100 g; NUTMEG OIL 0.15 g/100 g; TURPENTINE 0.05 g/100 g; CEDAR LEAF OIL 0.05 g/100 g; MINERAL OIL 0.05 g/100 g; THYMOL 0.05 g/100 g

AVEDANA® MEDICATED CHEST RUB

Active Ingredients

Ingredients Purpose

Camphor 4.8% cough suppressant/topical analgesic

Eucalyptus Oil 1.2% cough suppressant

Menthol 2.6% cough supressant/topical analgesic

Uses

Uses - On chest and throat, temporarily relieves cough due to common cold. On the muscles and joints, temporarily relieves minor aches and pains.

Warnings

For external use only. Avoid contact with eyes.

Do not use - by mouth - in nostrils - on wounds or damaged skin - with tight bandages

Ask a doctor before use if you have

asthma - excessive phlegm (mucus) - emphysema - persistent or chronic cough - cough associated with smoking

If pregnant or breast-feeding, ask a health professional before use.

Keep out of reach of children

In case of accidental ingestion, get medical help or contact Poison Control Center immediately.

Directions

- children under 2 years of age, ask a doctor before using the product - adults and children 2 years and older: rub a thick layer on throat and chest or rub on sore aching muscles. If desired cover with a dry soft cloth, but keep clothing loose. Repeat up to 3 times a day.

Other information

store at room temperature

Other Ingredients

Petrolatum, Mineral Oil, Nutmeg Oil, Turpentine Oil, Cedar Leaf Oil, Thymol

Purpose

cough suppressant / topical analgesic, cough suppressant